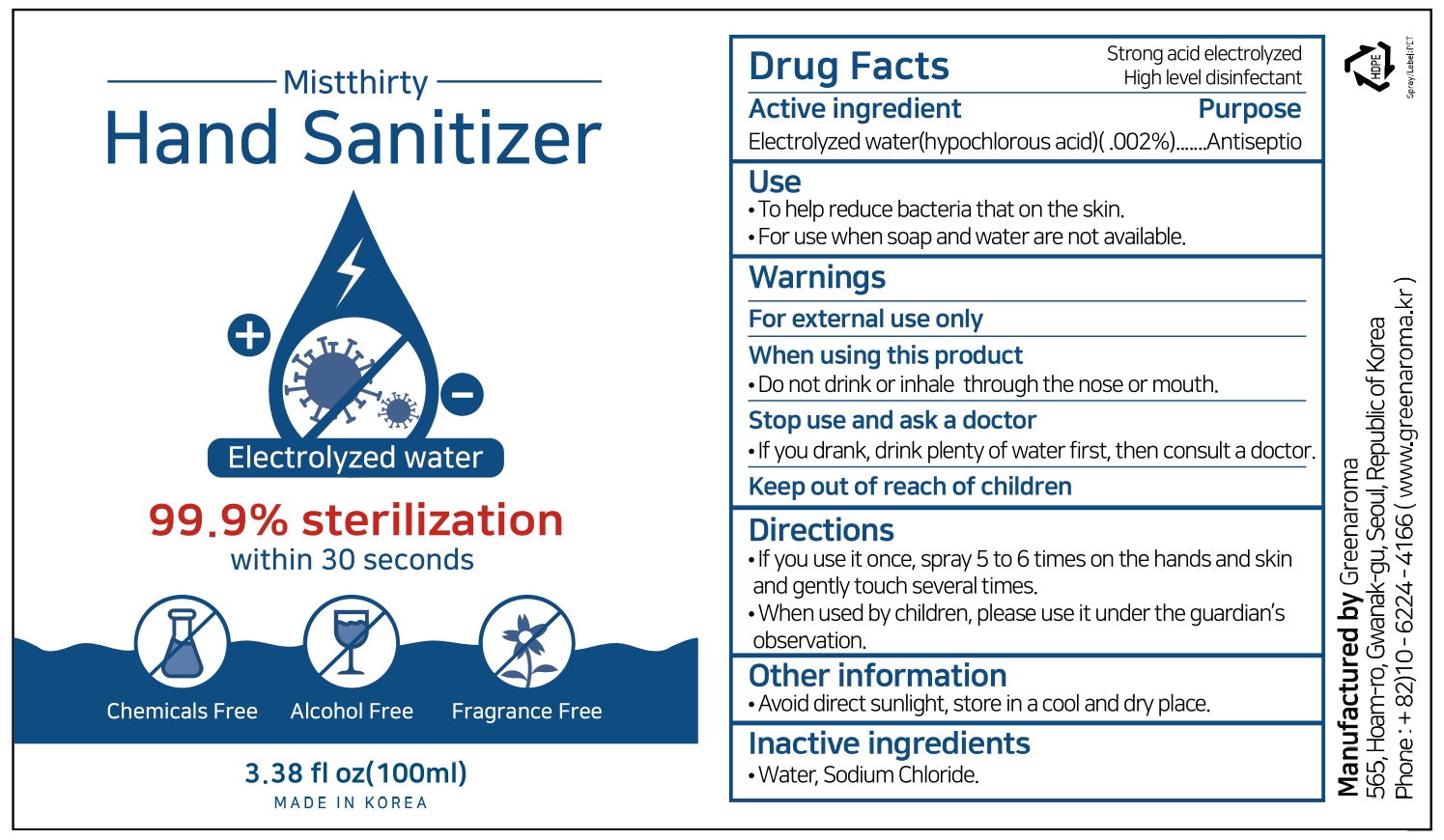 DRUG LABEL: MISTTHIRTY
NDC: 90054-201 | Form: LIQUID
Manufacturer: Green Aroma
Category: otc | Type: HUMAN OTC DRUG LABEL
Date: 20221229

ACTIVE INGREDIENTS: HYPOCHLOROUS ACID 0.002 g/100 mL
INACTIVE INGREDIENTS: WATER; SODIUM CHLORIDE

Active ingredient

Electrolyzed water (hypochlorous acid) (.002%)

Purpose

Antiseptic

Use

To help reduce bacteria that on the skin.

For use when soap and water are not available.

Warnings

For external use only

When using this product

Do not drink or inhale through the nose or mouth.

Stop use and ask a doctor

If you drank, drink plenty of water first, then consult a doctor.

Directions

If you use it once, spray 5 to 6 times on the hands and skin and gently touch several times.

When used by children, please use it under the guardian's observation.

Other information

Avoid direct sunlight, store in a cool and dry place.

Inactive ingredients

Water, Sodium Chloride